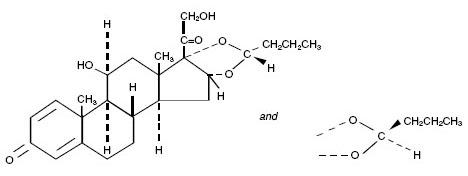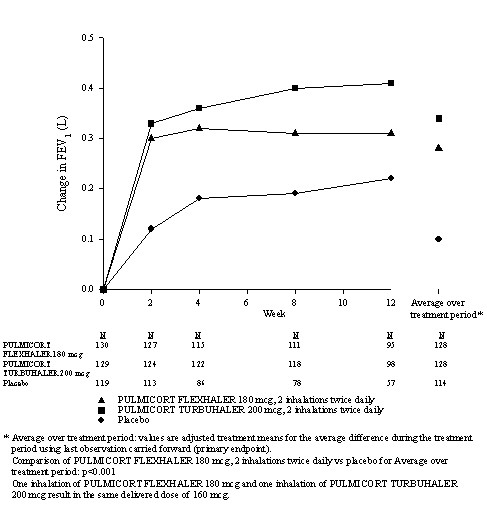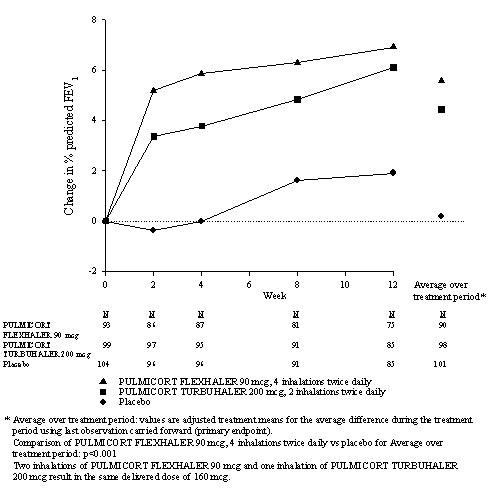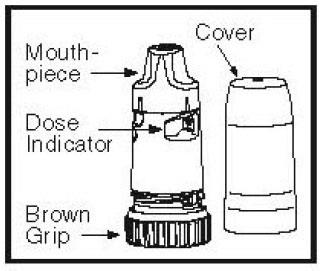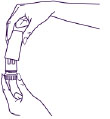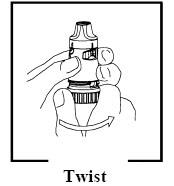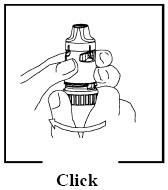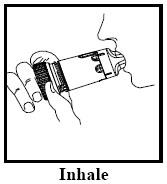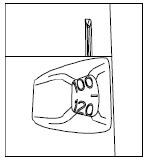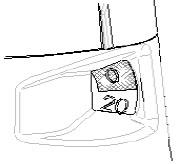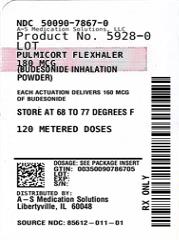 DRUG LABEL: PULMICORT
NDC: 50090-7867 | Form: AEROSOL, POWDER
Manufacturer: A-S Medication Solutions
Category: prescription | Type: HUMAN PRESCRIPTION DRUG LABEL
Date: 20260129

ACTIVE INGREDIENTS: BUDESONIDE 180 ug/1 1
INACTIVE INGREDIENTS: LACTOSE

HIGHLIGHTS OF PRESCRIBING INFORMATION

These highlights do not include all the information needed to use PULMICORT FLEXHALER™ safely and effectively. See full prescribing information for PULMICORT FLEXHALER.
PULMICORT FLEXHALER™ (budesonide) inhalation powder
Initial U.S. Approval: 2006

1 INDICATIONS AND USAGE

PULMICORT FLEXHALER is a corticosteroid indicated for:

- Maintenance treatment of asthma as prophylactic therapy in adult and pediatric patients six years of age or older (1)

Limitations of Use:

Not indicated for the relief of acute bronchospasm (1)

2 DOSAGE AND ADMINISTRATION

For oral inhalation only.

- Patients 18 Years of Age and Older: For patients 18 years of age and older, the recommended starting dosage is 360 mcg twice daily. In some adult patients, a starting dose of 180 mcg twice daily may be adequate. The maximum dosage should not exceed 720 mcg twice daily (2.1)
- Patients 6 to 17 Years of Age: The recommended starting dosage is 180 mcg twice daily. In some pediatric patients, a starting dose of 360 mcg twice daily may be appropriate. The maximum dosage should not exceed 360 mcg twice daily (2.1)

3 DOSAGE FORMS AND STRENGTHS

FLEXHALER device containing budesonide (90 mcg or 180 mcg) as an inhalation powder (3)

4 CONTRAINDICATIONS

- Primary treatment of status asthmaticus or other acute episodes of asthma where intensive measures are required (4)
- Severe hypersensitivity to milk proteins and any of the ingredients in PULMICORT FLEXHALER (4)

5 WARNINGS AND PRECAUTIONS

- Localized Infections: Candida albicans infection of the mouth and throat may occur. Monitor patients periodically for signs of adverse effects on the oral cavity. Advise patients to rinse the mouth following inhalation (5.1)
- Deterioration of Asthma or Acute Episodes: PULMICORT FLEXHALER should not be used for relief of acute symptoms. Patients require immediate re-evaluation during rapidly deteriorating asthma (5.2)
- Hypersensitivity Reactions: Anaphylaxis, rash, contact dermatitis, urticaria, angioedema, and bronchospasm have been reported with use of PULMICORT FLEXHALER. Discontinue PULMICORT FLEXHALER if such reactions occur (5.3)
- Immunosuppression: Potential worsening of infections (e.g., existing tuberculosis, fungal, bacterial, viral, or parasitic infection; or ocular herpes simplex). Use with caution in patients with these infections. More serious or even fatal course of chickenpox or measles can occur in susceptible patients (5.4)
- Transferring Patients from Systemic Corticosteroid Therapy: Risk of impaired adrenal function when transferring from oral steroids. Taper patients slowly from systemic corticosteroids if transferring to PULMICORT FLEXHALER (5.5)
- Hypercorticism and Adrenal Suppression: May occur with very high dosages or at the regular dosage in susceptible individuals. If such changes occur, reduce PULMICORT FLEXHALER slowly (5.6)
- Reduction in Bone Mineral Density with Long term Administration: Monitor patients with major risk factors for decreased bone mineral content (5.8)
- Effects on Growth: Monitor growth of pediatric patients (5.9)
- Glaucoma and Cataracts: Close monitoring is warranted (5.10)
- Paradoxical Bronchospasm: Discontinue PULMICORT FLEXHALER and institute alternative therapy if paradoxical bronchospasm occurs (5.11)
- Eosinophilic Conditions and Churg-Strauss Syndrome: Be alert to eosinophilic conditions (5.12)

6 ADVERSE REACTIONS

Most common adverse reactions (incidence ≥1%) are nasopharyngitis, nasal congestion, pharyngitis, rhinitis allergic, viral upper respiratory tract infection, nausea, viral gastroenteritis, otitis media, oral candidiasis (6.1)

To report SUSPECTED ADVERSE REACTIONS, contact the Safety Call Center at 1-888-994-8116 or FDA at 1-800-FDA-1088 or www.fda.gov/medwatch

7 DRUG INTERACTIONS

- Strong Cytochrome P450 3A4 Inhibitors (e.g., ritonavir): Use with caution. May cause increased systemic corticosteroid effects (5.7, 7.1)

FULL PRESCRIBING INFORMATION

1 INDICATIONS AND USAGE

1.1 Treatment of Asthma

PULMICORT FLEXHALER is indicated for the maintenance treatment of asthma as prophylactic therapy in patients six years of age or older.

Limitations of Use:

- PULMICORT FLEXHALER is NOT indicated for the relief of acute bronchospasm.

2 DOSAGE AND ADMINISTRATION

PULMICORT FLEXHALER should be administered twice daily by the orally inhaled route only. After inhalation, the patient should rinse the mouth with water without swallowing [see Patient Counseling Information (17.1)].

Patients should be instructed to prime PULMICORT FLEXHALER prior to its initial use, and instructed to inhale deeply and forcefully each time the device is used.

The safety and efficacy of PULMICORT FLEXHALER when administered in excess of recommended doses have not been established.

After asthma stability has been achieved, it is desirable to titrate to the lowest effective dosage to reduce the possibility of side effects. For patients who do not respond adequately to the starting dose after 1-2 weeks of therapy with PULMICORT FLEXHALER, increasing the dose may provide additional asthma control.

2.1 Asthma

If asthma symptoms arise in the period between doses, an inhaled, short-acting beta2-agonist should be taken for immediate relief.

Patients 18 Years of Age and Older: For patients 18 years of age and older, the recommended starting dosage is 360 mcg twice daily. In some adult patients, a starting dose of 180 mcg twice daily may be adequate. The maximum dosage should not exceed 720 mcg twice daily.

Patients 6 to 17 Years of Age: The recommended starting dosage is 180 mcg twice daily. In some pediatric patients, a starting dose of 360 mcg twice daily may be appropriate. The maximum dosage should not exceed 360 mcg twice daily.

For all patients, it is desirable to titrate to the lowest effective dose after adequate asthma stability is achieved.

Improvement in asthma control following inhaled administration of budesonide can occur within 24 hours of initiation of treatment, although maximum benefit may not be achieved for 1 to 2 weeks, or longer. Individual patients will experience a variable onset and degree of symptom relief.

If a previously effective dosage regimen of PULMICORT FLEXHALER fails to provide adequate control of asthma, the therapeutic regimen should be re-evaluated and additional therapeutic options (e.g., replacing the lower strength of PULMICORT FLEXHALER with the higher strength or initiating oral corticosteroids) should be considered.

3 DOSAGE FORMS AND STRENGTHS

PULMICORT FLEXHALER is available as a dry powder for inhalation containing budesonide in the following 2 strengths: 90 mcg and 180 mcg. Each inhaler contains 60 or 120 actuations.

4 CONTRAINDICATIONS

The use of PULMICORT FLEXHALER is contraindicated in the following conditions:

- Primary treatment of status asthmaticus or other acute episodes of asthma where intensive measures are required.
- Severe hypersensitivity to milk proteins or any ingredients of PULMICORT FLEXHALER [see Warnings and Precautions (5.3), Description (11)].

5 WARNINGS AND PRECAUTIONS

5.1 Local Effects

In clinical studies, the development of localized infections of the mouth and pharynx with Candida albicans has occurred in patients treated with PULMICORT FLEXHALER. When such an infection develops, it should be treated with appropriate local or systemic (i.e., oral antifungal) therapy while treatment with PULMICORT FLEXHALER continues, but at times, therapy with PULMICORT FLEXHALER may need to be interrupted. Patients should rinse the mouth after inhalation of PULMICORT FLEXHALER.

5.2 Deterioration of Asthma or Acute Episodes

PULMICORT FLEXHALER is not a bronchodilator and is not indicated for the rapid relief of bronchospasm or other acute episodes of asthma. Patients should be instructed to contact their physician immediately if episodes of asthma not responsive to their usual doses of bronchodilators occur during the course of treatment with PULMICORT FLEXHALER. During such episodes, patients may require therapy with oral corticosteroids.

An inhaled short acting beta2-agonist, not PULMICORT FLEXHALER, should be used to relieve acute symptoms such as shortness of breath. When prescribing PULMICORT FLEXHALER, the physician must also provide the patient with an inhaled, short-acting beta2-agonist (e.g., albuterol) for treatment of acute symptoms, despite regular twice-daily (morning and evening) use of PULMICORT FLEXHALER.

5.3 Hypersensitivity Reactions Including Anaphylaxis

Hypersensitivity reactions including anaphylaxis, rash, contact dermatitis, urticaria, angioedema, and bronchospasm have been reported with use of PULMICORT FLEXHALER. Discontinue PULMICORT FLEXHALER if such reactions occur [see Contraindications (4), Adverse Reactions (6)].

PULMICORT FLEXHALER contains small amounts of lactose, which contains trace levels of milk proteins. It is possible that cough, wheezing, or bronchospasm may occur in patients who have a severe milk protein allergy [see Contraindications (4), Adverse Reactions (6.2)].

5.4 Immunosuppression

Patients who are on drugs that suppress the immune system are more susceptible to infection than healthy individuals. Chicken pox and measles, for example, can have a more serious or even fatal course in susceptible children or adults using corticosteroids. In children or adults who have not had these diseases or been properly immunized, particular care should be taken to avoid exposure. How the dose, route, and duration of corticosteroid administration affects the risk of developing a disseminated infection is not known. The contribution of the underlying disease and/or prior corticosteroid treatment to the risk is also not known. If exposed to chicken pox, therapy with varicella zoster immune globulin (VZIG) or pooled intravenous immunoglobulin (IVIG), as appropriate, may be indicated. If exposed to measles, prophylaxis with pooled intramuscular immunoglobulin (IG) may be indicated (see the respective package inserts for complete VZIG and IG prescribing information). If chicken pox develops, treatment with antiviral agents may be considered. The immune responsiveness to varicella vaccine was evaluated in pediatric patients with asthma ages 12 months to 8 years with budesonide inhalation suspension.

An open-label, nonrandomized clinical study examined the immune responsiveness to varicella vaccine in 243 asthma patients 12 months to 8 years of age who were treated with budesonide inhalation suspension 0.25 mg to 1 mg daily (n=151) or non-corticosteroid asthma therapy (n=92) (i.e., beta2-agonists, leukotriene receptor antagonists, cromones). The percentage of patients developing a seroprotective antibody titer of ≥5.0 (gpELISA value) in response to the vaccination was similar in patients treated with budesonide inhalation suspension (85%), compared to patients treated with non-corticosteroid asthma therapy (90%). No patient treated with budesonide inhalation suspension developed chicken pox as a result of vaccination.

Inhaled corticosteroids should be used with caution, if at all, in patients with active or quiescent tuberculosis infection of the respiratory tract, untreated systemic fungal, bacterial, viral or parasitic infections, or ocular herpes simplex.

5.5 Transferring Patients from Systemic Corticosteroid Therapy

Particular care is needed for patients who are transferred from systemically active corticosteroids to PULMICORT FLEXHALER because deaths due to adrenal insufficiency have occurred in asthmatic patients during and after transfer from systemic corticosteroids to less systemically available inhaled corticosteroids. After withdrawal from systemic corticosteroids, a number of months are required for recovery of hypothalamic-pituitary-adrenal (HPA) function.

Patients who have been previously maintained on 20 mg or more per day of prednisone (or its equivalent) may be most susceptible, particularly when their systemic corticosteroids have been almost completely withdrawn.

During this period of HPA suppression, patients may exhibit signs and symptoms of adrenal insufficiency when exposed to trauma, surgery, or infection (particularly gastroenteritis) or other conditions associated with severe electrolyte loss. Although PULMICORT FLEXHALER may provide control of asthma symptoms during these episodes, in recommended doses it supplies less than normal physiological amounts of glucocorticoid systemically and does NOT provide the mineralocorticoid activity that is necessary for coping with these emergencies.

During periods of stress or a severe asthma attack, patients who have been withdrawn from systemic corticosteroids should be instructed to resume oral corticosteroids (in large doses) immediately and to contact their physicians for further instruction. These patients should also be instructed to carry a medical identification card indicating that they may need supplementary systemic corticosteroids during periods of stress or a severe asthma attack.

Patients requiring oral corticosteroids should be weaned slowly from systemic corticosteroid use after transferring to PULMICORT FLEXHALER. Prednisone reduction can be accomplished by reducing the daily prednisone dose by 2.5 mg on a weekly basis during therapy with PULMICORT FLEXHALER. Lung function (mean forced expiratory volume in 1 second [FEV1] or morning peak expiratory flow [PEF]), beta-agonist use, and asthma symptoms should be carefully monitored during withdrawal of oral corticosteroids. In addition to monitoring asthma signs and symptoms, patients should be observed for signs and symptoms of adrenal insufficiency such as fatigue, lassitude, weakness, nausea and vomiting, and hypotension.

Transfer of patients from systemic corticosteroid therapy to PULMICORT FLEXHALER may unmask allergic conditions previously suppressed by the systemic corticosteroid therapy, (e.g., rhinitis, conjunctivitis, eczema, arthritis, eosinophilic conditions). Some patients may experience symptoms of systemically active corticosteroid withdrawal (e.g., joint and/or muscular pain, lassitude, depression) despite maintenance or even improvement of respiratory function.

5.6 Hypercorticism and Adrenal Suppression

PULMICORT FLEXHALER will often help control asthma symptoms with less suppression of HPA function than therapeutically equivalent oral doses of prednisone. Since budesonide is absorbed into the circulation and can be systemically active at higher doses, the beneficial effects of PULMICORT FLEXHALER in minimizing HPA dysfunction may be expected only when recommended dosages are not exceeded and individual patients are titrated to the lowest effective dose. Since individual sensitivity to effects on cortisol production exists, physicians should consider this information when prescribing PULMICORT FLEXHALER.

Because of the possibility of systemic absorption of inhaled corticosteroids, patients treated with PULMICORT FLEXHALER should be observed carefully for any evidence of systemic corticosteroid effects. Particular care should be taken in observing patients postoperatively or during periods of stress for evidence of inadequate adrenal response.

It is possible that systemic corticosteroid effects such as hypercorticism and adrenal suppression (including adrenal crisis) may appear in a small number of patients, particularly when budesonide is administered at higher than recommended doses over prolonged periods of time. If such effects occur, the dosage of PULMICORT FLEXHALER should be reduced slowly, consistent with accepted procedures for reducing systemic corticosteroids and for management of asthma symptoms.

5.7 Interactions with Strong Cytochrome P450 3A4 Inhibitors

Caution should be exercised when considering the co-administration of PULMICORT FLEXHALER with ketoconazole, and other known strong CYP3A4 inhibitors (e.g., ritonavir, atazanavir, clarithromycin, indinavir, itraconazole, nefazodone, nelfinavir, saquinavir, telithromycin) because adverse effects related to increased systemic exposure to budesonide may occur [see Drug Interactions (7.1), Clinical Pharmacology (12.3)].

5.8 Reduction in Bone Mineral Density

Decreases in bone mineral density (BMD) have been observed with long-term administration of products containing inhaled corticosteroids. The clinical significance of small changes in BMD with regard to long-term consequences such as fracture is unknown. Patients with major risk factors for decreased bone mineral content, such as prolonged immobilization, family history of osteoporosis, post menopausal status, tobacco use, advance age, poor nutrition, or chronic use of drugs that can reduce bone mass (e.g., anticonvulsants, oral corticosteroids) should be monitored and treated with established standards of care.

5.9 Effects on Growth

Orally inhaled corticosteroids, including budesonide, may cause a reduction in growth velocity when administered to pediatric patients. Monitor the growth of pediatric patients receiving PULMICORT FLEXHALER routinely (e.g., via stadiometry). To minimize the systemic effects of orally inhaled corticosteroids, including PULMICORT FLEXHALER, titrate each patient’s dose to the lowest dosage that effectively controls his/her symptoms [see Dosage and Administration (2.1), Use in Specific Populations (8.4)].

5.10 Glaucoma and Cataracts

Glaucoma, increased intraocular pressure, and cataracts have been reported following the long-term administration of inhaled corticosteroids, including budesonide. Therefore, close monitoring is warranted in patients with a change in vision or with a history of increased intraocular pressure, glaucoma, and/or cataracts.

5.11 Paradoxical Bronchospasm and Upper Airway Symptoms

As with other inhaled asthma medications, PULMICORT FLEXHALER can produce paradoxical bronchospasm, which may be life threatening. If paradoxical bronchospasm occurs following dosing with PULMICORT FLEXHALER, it should be treated immediately with an inhaled, short-acting beta2-bronchodilator. PULMICORT FLEXHALER should be discontinued immediately, and alternative therapy should be instituted.

5.12 Eosinophilic Conditions and Churg-Strauss Syndrome

In rare cases, patients on inhaled corticosteroids may present with systemic eosinophilic conditions. Some of these patients have clinical features of vasculitis consistent with Churg-Strauss syndrome, a condition that is often treated with systemic corticosteroid therapy. These events usually, but not always, have been associated with the reduction and/or withdrawal of oral corticosteroid therapy following the introduction of inhaled corticosteroids. Physicians should be alert to eosinophilia, vasculitic rash, worsening pulmonary symptoms, cardiac complications, and/or neuropathy presenting in their patients. A causal relationship between budesonide and these underlying conditions has not been established.

6 ADVERSE REACTIONS

Systemic and inhaled corticosteroid use may result in the following:

- Candida albicans Infection [see Warnings and Precautions (5.1)]
- Hypersensitivity Including Anaphylaxis [see Warnings and Precautions (5.3)]
- Immunosuppression [see Warnings and Precautions (5.4)]
- Hypercorticism and Adrenal Suppression [see Warnings and Precautions (5.6)]
- Reduction in Bone Mineral Density [see Warnings and Precautions (5.8)]
- Growth Effects [see Warnings and Precautions (5.9), Use in Specific Populations (8.4)]
- Glaucoma and Cataracts [see Warnings and Precautions (5.10)]
- Eosinophilic Conditions and Churg-Strauss [see Warnings and Precautions (5.12)]

6.1 Clinical Trials Experience

Because clinical trials are conducted under widely varying conditions, adverse reaction rates observed in the clinical trials of a drug cannot be directly compared to rates in the clinical trials of another drug and may not reflect the rates observed in practice.

PULMICORT FLEXHALER

Patients 6 years and older

The incidence of common adverse reactions in Table 1 is based upon pooled data reported in patients treated with PULMICORT FLEXHALER 180 or 90 mcg in two double-blind, placebo-controlled clinical trials in which 226 patients (106 females and 120 males) with mild to moderate asthma, previously receiving bronchodilators, inhaled corticosteroids, or both, were treated with PULMICORT FLEXHALER, administered as 360 mcg twice daily for 12 weeks. In these trials, the patients on PULMICORT FLEXHALER had a mean age of 28 years (range 6-80 years) and were predominantly Caucasian (59.7%) and Asian (31.4%). Table 1 includes all adverse reactions (regardless of investigator causality assessment) that occurred at a rate of ≥1% in the PULMICORT FLEXHALER group and more commonly than the placebo group.

Table 1 - Adverse Reactions occurring at an incidence of ≥1% and more commonly than placebo in the PULMICORT FLEXHALER group: pooled data from two 12-week, double-blind, placebo-controlled clinical asthma trials in patients 6 years and older
Adverse Event | PULMICORT FLEXHALER; 360 mcg twice daily; N=226; % | Placebo; N=230; %
Nasopharyngitis | 9.3 | 8.3
Nasal congestion | 2.7 | 0.4
Pharyngitis | 2.7 | 1.7
Rhinitis allergic | 2.2 | 1.3
Viral upper respiratory tract infection | 2.2 | 1.3
Nausea | 1.8 | 0.9
Viral gastroenteritis | 1.8 | 0.4
Otitis media | 1.3 | 0.9
Oral candidiasis | 1.3 | 0.4
Average exposure duration (days) | 76.2 | 68.2

Long-Term Safety in Patients 6 years of age and older

Non-placebo controlled long-term studies in children (at doses up to 360 mcg daily), and adolescent and adult subjects (at doses up to 720 mcg daily), treated for up to one year with PULMICORT FLEXHALER, revealed a similar pattern and incidence of adverse events.

PULMICORT TURBUHALER; a different PULMICORT DPI

The following adverse reactions occurred in placebo-controlled clinical trials with similar or lower doses with inhaled budesonide via a different PULMICORT dry powder inhaler with an incidence of ≥1% in the budesonide group and were more common than in the placebo group:

≥3%: respiratory infection, sinusitis, headache, pain, back pain, fever.

≥1-3%: neck pain, syncope, abdominal pain, dry mouth, vomiting, weight gain, fracture, myalgia, hypertonia, migraine, ecchymosis, insomnia, infection, taste perversion, voice alteration.

Higher doses of inhaled budesonide (800 mcg twice daily) via a different PULMICORT dry powder inhaler resulted in an increased incidence of voice alteration, flu syndrome, dyspepsia, gastroenteritis, nausea, and back pain, compared with doses of 400 mcg twice daily.

In a 20-week trial in adult asthmatics who previously required oral corticosteroids, the incidence of adverse reactions was evaluated with 400 mcg twice daily (N=53) and 800 mcg twice daily (N=53) of inhaled budesonide via a different PULMICORT dry powder inhaler and compared with placebo (N=53). In considering these data, the increased average duration of exposure for inhaled budesonide patients (78 days for inhaled budesonide vs. 41 days for placebo) should be taken into account. Adverse reactions, regardless of investigator causality assessment, reported in more than five patients in the budesonide group and which occurred more commonly than the placebo group in decreasing order of frequency include: respiratory infection, sinusitis, headache, oral candidiasis, pain, asthenia, dyspepsia, arthralgia, cough increased, nausea and rhinitis.

6.2 Postmarketing Experience

The following adverse reactions have been reported during post-approval use of PULMICORT FLEXHALER. Because these reactions are reported voluntarily from a population of uncertain size, it is not always possible to reliably estimate their frequency or establish a causal relationship to drug exposure.

Immune system disorders: immediate and delayed hypersensitivity reactions including anaphylactic reaction, angioedema, bronchospasm, rash, contact dermatitis, urticaria, and cough, wheezing or bronchospasm in patients with severe milk protein hypersensitivity [see Warnings and Precautions (5.3), Contraindications (4)]

Endocrine disorders: symptoms of hypocorticism and hypercorticism [see Warnings and Precautions (5.6)]

Eye disorders: cataracts, glaucoma, increased intraocular pressure [see Warnings and Precautions (5.10)]

Psychiatric disorders: psychiatric symptoms including psychosis, depression, aggressive reactions, irritability, nervousness, restlessness, and anxiety

Respiratory, thoracic, and mediastinal disorders: throat irritation

Skin and subcutaneous tissue disorders: skin bruising

7 DRUG INTERACTIONS

7.1 Inhibitors of Cytochrome P450 3A4

The main route of metabolism of corticosteroids, including budesonide, is via cytochrome P450 (CYP) isoenzyme 3A4 (CYP3A4). After oral administration of ketoconazole, a strong inhibitor of CYP3A4, the mean plasma concentration of orally administered budesonide increased. Concomitant administration of CYP3A4 may inhibit the metabolism of, and increase the systemic exposure to, budesonide. Caution should be exercised when considering the co-administration of PULMICORT FLEXHALER with long-term ketoconazole and other known strong CYP3A4 inhibitors (e.g., ritonavir, atazanavir, clarithromycin, indinavir, itraconazole, nefazodone, nelfinavir, saquinavir, telithromycin) [see Warnings and Precautions (5.7)].

8 USE IN SPECIFIC POPULATIONS

8.1 Pregnancy

Risk Summary

There are no adequate well-controlled studies of PULMICORT FLEXHALER in pregnant women. However, there are published studies on the use of budesonide, the active ingredient in PULMICORT FLEXHALER, in pregnant women. In animal reproduction studies, budesonide, administered by the subcutaneous route, caused structural abnormalities, was embryocidal, and reduced fetal weights in rats and rabbits at less than the maximum recommended human daily inhalation dose (MRHDID), but these effects were not seen in rats that received inhaled doses approximately 2 times the MRHDID (see Data). Studies of pregnant women have not shown that inhaled budesonide increases the risk of abnormalities when administered during pregnancy. Experience with oral corticosteroids suggests that rodents are more prone to structural abnormalities from corticosteroid exposure than humans.

The estimated background risk of major birth defects and miscarriage of the indicated populations is unknown. In the U.S. general population, the estimated background risk of major birth defects and miscarriage in clinically recognized pregnancies is 2% to 4% and 15% to 20%, respectively.

Clinical Considerations

Disease-Associated Maternal and/or Embryo/Fetal risk

In women with poorly or moderately controlled asthma, there is an increased risk of several perinatal adverse outcomes such as preeclampsia in the mother and prematurity, low birth weight, and small for gestational age in the neonate. Pregnant women with asthma should be closely monitored and medication adjusted as necessary to maintain optimal asthma control.

Labor or Delivery

There are no well-controlled human studies that have investigated the effects of PULMICORT FLEXHALER during labor and delivery.

Data

Human Data

Studies of pregnant women have not shown that inhaled budesonide increases the risk of abnormalities when administered during pregnancy. The results from a large population-based prospective cohort epidemiological study reviewing data from three Swedish registries covering approximately 99% of the pregnancies from 1995-1997 (i.e., Swedish Medical Birth Registry; Registry of Congenital Malformations; Child Cardiology Registry) indicate no increased risk for congenital malformations from the use of inhaled budesonide during early pregnancy. Congenital malformations were studied in 2014 infants born to mothers reporting the use of inhaled budesonide for asthma in early pregnancy (usually 10-12 weeks after the last menstrual period), the period when most major organ malformations occur. The rate of recorded congenital malformations was similar compared to the general population rate (3.8% vs. 3.5%, respectively). In addition, after exposure to inhaled budesonide, the number of infants born with orofacial clefts was similar to the expected number in the normal population (4 children vs. 3.3, respectively).

These same data were utilized in a second study bringing the total to 2534 infants whose mothers were exposed to inhaled budesonide. In this study, the rate of congenital malformations among infants whose mothers were exposed to inhaled budesonide during early pregnancy was not different from the rate for all newborn babies during the same period (3.6%).

Animal Data

In a fertility and reproduction study, male rats were subcutaneously dosed for 9 weeks and females for 2 weeks prior to pairing and throughout the mating period. Females were dosed up until weaning of their offspring. Budesonide caused a decrease in prenatal viability and viability in the pups at birth and during lactation, along with a decrease in maternal body-weight gain, at doses 0.1 times the MRHDID (on a mcg/m^2 basis at maternal subcutaneous doses of 20 mcg/kg/day and above). No such effects were noted at a dose 0.03 times the MRHDID (on a mcg/m^2 basis at a maternal subcutaneous dose of 5 mcg/kg/day).

In an embryo-fetal development study in pregnant rabbits dosed during the period of organogenesis from gestation days 6-18, budesonide produced fetal loss, decreased fetal weight, and skeletal abnormalities at doses 0.3 times the MRHDID (on a mcg/m^2 basis at a maternal subcutaneous dose of 25 mcg/kg/day). In an embryo-fetal development study in pregnant rats dosed during the period of organogenesis from gestation days 6-15, budesonide produced similar adverse fetal effects at doses approximately 4 times the MRHDID (on a mcg/m^2 basis at a maternal subcutaneous dose of 500 mcg/kg/day). In another embryo-fetal development study in pregnant rats, no structural abnormalities or embryocidal effects were seen at doses approximately 2 times the MRHDID (on a mcg/m^2 basis at maternal inhalation doses up to 250 mcg/kg/day).

In a peri-and post-natal development study, rats dosed from gestation day 15 to postpartum day 21, budesonide had no effects on delivery, but did have an effect on growth and development of offspring. Offspring survival was reduced and surviving offspring had decreased mean body weights at birth and during lactation at doses 0.1 times the MRHDID and higher (on a mcg/m^2 basis at maternal subcutaneous doses of 20 mcg/kg/day and higher). These findings occurred in the presence of maternal toxicity.

8.2 Lactation

Risk Summary

There are no available data on the effects of PULMICORT FLEXHALER on the breastfed child or on milk production. Budesonide, like other inhaled corticosteroids, is present in human milk [see Data]. The developmental and health benefits of breastfeeding should be considered along with the mother’s clinical need for PULMICORT FLEXHALER and any potential adverse effects on the breastfed infant from PULMICORT FLEXHALER or from the underlying maternal condition.

Data

Human data with budesonide delivered via dry powder inhaler indicates that the total daily oral dose of budesonide available in breast milk to the infant is approximately 0.3% to 1% of the dose inhaled by the mother [see Clinical Pharmacology (12.3)].

8.4 Pediatric Use

In a 12-week pivotal study, 204 patients 6 to 17 years of age were treated with PULMICORT FLEXHALER twice daily [see Clinical Studies (14.1)]. Efficacy results in this age group were similar to those observed in patients 18 years and older. There were no obvious differences in the type or frequency of adverse events reported in this age group compared with patients 18 years of age and older.

The safety and effectiveness of PULMICORT FLEXHALER in asthma patients below 6 years of age have not been established.

Controlled clinical studies have shown that orally inhaled corticosteroids, including budesonide, may cause a reduction in growth velocity in pediatric patients. This effect has been observed in the absence of laboratory evidence of hypothalamic-pituitary-adrenal (HPA) axis suppression, suggesting that growth velocity is a more sensitive indicator of systemic corticosteroid exposure in pediatric patients than some commonly used tests of HPA-axis function. The long-term effects of this reduction in growth velocity associated with orally inhaled corticosteroids including the impact on final adult height are unknown. The potential for “catch up” growth following discontinuation of treatment with orally inhaled corticosteroids has not been adequately studied.

In a study of asthmatic children 5-12 years of age, those treated with inhaled budesonide via a different PULMICORT dry powder inhaler 200 mcg twice daily (n=311) had a 1.1-centimeter reduction in growth compared with those receiving placebo (n=418) at the end of one year; the difference between these two treatment groups did not increase further over three years of additional treatment. By the end of four years, children treated with a different PULMICORT dry powder inhaler and children treated with placebo had similar growth velocities. Conclusions drawn from this study may be confounded by the unequal use of corticosteroids in the treatment groups and inclusion of data from patients attaining puberty during the course of the study.

The administration of inhaled budesonide via a different PULMICORT dry-powder inhaler in doses up to 800 mcg/day (mean daily dose 445 mcg/day) or via a pressurized metered-dose inhaler in doses up to 1200 mcg/day (mean daily dose 620 mcg/day) to 216 pediatric patients (age 3 to 11 years) for 2 to 6 years had no significant effect on statural growth compared with non-corticosteroid therapy in 62 matched control patients. However, the long-term effect of inhaled budesonide on growth is not fully known.

The growth of pediatric patients receiving orally inhaled corticosteroids, including PULMICORT FLEXHALER, should be monitored (e.g., via stadiometry). If a child or adolescent on any corticosteroid appears to have growth suppression, the possibility that he/she is particularly sensitive to this effect should be considered. The potential growth effects of prolonged treatment should be weighed against clinical benefits obtained. To minimize the systemic effects of inhaled corticosteroids, including PULMICORT FLEXHALER, each patient should be titrated to the lowest dose that effectively controls his/her asthma [see Dosage and Administration (2)].

8.5 Geriatric Use

Of the total number of patients in controlled clinical studies receiving inhaled budesonide, 153 (n=11 treated with PULMICORT FLEXHALER) were 65 years of age or older and one was age 75 years or older. No overall differences in safety were observed between these patients and younger patients. Clinical studies did not include sufficient numbers of patients aged 65 years and over to determine differences in efficacy between elderly and younger patients. Other reported clinical or medical surveillance experience has not identified differences in responses between the elderly and younger patients. In general, dose selection for an elderly patient should be cautious, usually starting at the low end of the dosing range, reflecting the greater frequency of decreased hepatic, renal, or cardiac function, and of concomitant disease or other drug therapy.

8.6 Hepatic Impairment

Formal pharmacokinetic studies using PULMICORT FLEXHALER have not been conducted in patients with hepatic impairment. However, since budesonide is predominantly cleared by hepatic metabolism, impairment of liver function may lead to accumulation of budesonide in the plasma. Therefore, patients with hepatic disease should be closely monitored.

10 OVERDOSAGE

The potential for acute toxic effects following overdose of PULMICORT FLEXHALER is low. If used at excessive doses for prolonged periods, systemic corticosteroid effects such as hypercorticism may occur [see Warnings and Precautions (5.6)]. Another budesonide-containing dry powder inhaler at 3200 mcg daily administered for 6 weeks caused a significant reduction (27%) in the plasma cortisol response to a 6-hour infusion of ACTH compared with placebo (+1%). The corresponding effect of 10 mg prednisone daily was a 35% reduction in the plasma cortisol response to ACTH.

Postmarketing experience showed that acute overdose of inhaled budesonide commonly remained asymptomatic. The use of excessive doses (up to 6400 mcg daily) for prolonged periods showed systemic corticosteroid effects such as hypercorticism.

11 DESCRIPTION

Budesonide, the active component of PULMICORT FLEXHALER, is a corticosteroid designated chemically as (RS)-11β, 16α, 17,21-Tetrahydroxypregna-1,4-diene-3,20-dione cyclic 16,17-acetal with butyraldehyde. Budesonide is provided as a mixture of two epimers (22R and 22S). The empirical formula of budesonide is C25H34O6 and its molecular weight is 430.5. Its structural formula is:

Budesonide is a white to off-white, tasteless, odorless powder that is practically insoluble in water and in heptane, sparingly soluble in ethanol, and freely soluble in chloroform. Its partition coefficient between octanol and water at pH 7.4 is 1.6 x 10^3.

PULMICORT FLEXHALER is an inhalation-driven multi-dose dry powder inhaler containing a formulation of 1 mg per actuation of micronized budesonide and micronized lactose monohydrate which contains trace levels of milk proteins [see Contraindications (4), Adverse Reactions (6.2)]. Each actuation of PULMICORT FLEXHALER 180 mcg delivers 160 mcg budesonide from the mouthpiece and each actuation of PULMICORT FLEXHALER 90 mcg delivers 80 mcg budesonide from the mouthpiece (based on in vitro testing at 60 L/min for 2 sec). Each PULMICORT FLEXHALER 180 mcg contains 120 actuations and each PULMICORT FLEXHALER 90 mcg contains 60 actuations.

In vitro testing has shown that the dose delivery for PULMICORT FLEXHALER is dependent on airflow through the device, as evidenced by a decrease in the fine particle dose at a flow rate of 30 L/min to a value that is approximately 40-50% of that produced at 60 L/min. At a flow rate of 40 L/min, the fine particle dose is approximately 70% of that produced at 60 L/min. Patient factors such as inspiratory flow rates will also affect the dose delivered to the lungs of patients in actual use [see Patient Information and Instructions for Use]. In asthmatic children age 6 to 17 (N=516, FEV1 2.29 [0.97– 4.28]) peak inspiratory flow (PIF) through PULMICORT FLEXHALER was 72.5 [19.1 – 103.6] L/min). Inspiratory flows were not measured in the adult pivotal study. Patients should be carefully instructed on the use of this drug product to assure optimal dose delivery.

12 CLINICAL PHARMACOLOGY

12.1 Mechanism of Action

Budesonide is an anti-inflammatory corticosteroid that exhibits potent glucocorticoid activity and weak mineralocorticoid activity. In standard in vitro and animal models, budesonide has approximately a 200-fold higher affinity for the glucocorticoid receptor and a 1000-fold higher topical anti-inflammatory potency than cortisol (rat croton oil ear edema assay). As a measure of systemic activity, budesonide is 40 times more potent than cortisol when administered subcutaneously and 25 times more potent when administered orally in the rat thymus involution assay. The clinical significance of this is unknown.

The activity of PULMICORT FLEXHALER is due to the parent drug, budesonide. In glucocorticoid receptor affinity studies, the 22R form was two times as active as the 22S epimer. In vitro studies indicated that the two forms of budesonide do not interconvert.

The precise mechanism of corticosteroid actions on inflammation in asthma is not known. Inflammation is an important component in the pathogenesis of asthma. Corticosteroids have a wide range of inhibitory activities against multiple cell types (e.g., mast cells, eosinophils, neutrophils, macrophages, and lymphocytes) and mediators (e.g., histamine, eicosanoids, leukotrienes, and cytokines) involved in allergic and non-allergic-mediated inflammation. These anti-inflammatory actions of corticosteroids may contribute to their efficacy in asthma.

Studies in asthmatic patients have shown a favorable ratio between topical anti-inflammatory activity and systemic corticosteroid effects over a wide range of doses of inhaled budesonide. This is explained by a combination of a relatively high local anti-inflammatory effect, extensive first pass hepatic degradation of orally absorbed drug (85-95%), and the low potency of formed metabolites (see below).

12.2 Pharmacodynamics

To confirm that systemic absorption is not a significant factor in the clinical efficacy of inhaled budesonide, a clinical study in patients with asthma was performed comparing 400 mcg budesonide administered via a pressurized metered-dose inhaler with a tube spacer to 1400 mcg of oral budesonide and placebo. The study demonstrated the efficacy of inhaled budesonide but not orally administered budesonide, even though systemic budesonide exposure was comparable for both treatments, indicating that the inhaled treatment is working locally in the lung. Thus, the therapeutic effect of conventional doses of orally inhaled budesonide are largely explained by its direct action on the respiratory tract.

Inhaled budesonide has been shown to decrease airway reactivity in various challenge models, including histamine, methacholine, sodium metabisulfite, and adenosine monophosphate in patients with hyperreactive airways. The clinical relevance of these models is not certain.

Pre-treatment with inhaled budesonide 1600 mcg daily (800 mcg twice daily) for 2 weeks reduced the acute (early-phase reaction) and delayed (late-phase reaction) decrease in FEV1 following inhaled allergen challenge.

HPA Axis effects: The effects of inhaled budesonide on the hypothalamic-pituitary-adrenal (HPA) axis were studied in 905 adults and 404 pediatric patients with asthma. For most patients, the ability to increase cortisol production in response to stress, as assessed by cosyntropin (ACTH) stimulation test, remained intact with inhaled budesonide treatment at recommended doses. For adult patients treated with 100, 200, 400, or 800 mcg twice daily for 12 weeks, 4%, 2%, 6%, and 13% respectively, had an abnormal stimulated cortisol response (peak cortisol <14.5 mcg/dL assessed by liquid chromatography following short-cosyntropin test) as compared with 8% of patients treated with placebo. Similar results were obtained in pediatric patients. In another study in adults, doses of 400, 800 and 1600 mcg of inhaled budesonide twice daily for 6 weeks were examined; 1600 mcg twice daily (twice the maximum recommended dose) resulted in a 27% reduction in stimulated cortisol (6-hour ACTH infusion) while 10 mg prednisone resulted in a 35% reduction. In this study, no patient taking doses of 400 and 800 mcg twice daily met the criterion for an abnormal stimulated cortisol response (peak cortisol <14.5 mcg/dL assessed by liquid chromatography) following ACTH infusion. An open-label, long-term follow-up of 1133 patients for up to 52 weeks confirmed the minimal effect on the HPA axis (both basal and stimulated plasma cortisol) of inhaled budesonide when administered at doses ranging from 100 to 800 mcg twice daily. In patients who had previously been oral steroid-dependent, use of inhaled budesonide at doses ranging from 100 to 800 mcg twice daily was associated with higher stimulated cortisol response compared with baseline following 1 year of therapy.

12.3 Pharmacokinetics

Absorption

After oral administration of budesonide, peak plasma concentration was achieved in about 1 to 2 hours and the absolute systemic availability was 6-13%. In contrast, most of budesonide delivered to the lungs is systemically absorbed. In healthy subjects, 34% of the metered dose was deposited in the lungs (as assessed by plasma concentration method and using a different budesonide containing dry-powder inhaler) with an absolute systemic availability of 39% of the metered dose. Peak steady-state plasma concentrations of budesonide delivered from PULMICORT FLEXHALER in adults with asthma (n=39) occurred at approximately 10 minutes post-dose and averaged 0.6 and 1.6 nmol/L at doses of 180 mcg once daily and 360 mcg twice daily, respectively.

In asthmatic patients, budesonide showed a linear increase in AUC and Cmax with increasing dose after both a single dose and repeated dosing of inhaled budesonide.

Distribution

The volume of distribution of budesonide was approximately 3 L/kg. It was 85-90% bound to plasma proteins. Protein binding was constant over the concentration range (1-100 nmol/L) achieved with, and exceeding, recommended doses of PULMICORT FLEXHALER. Budesonide showed little or no binding to corticosteroid binding globulin. Budesonide rapidly equilibrated with red blood cells in a concentration independent manner with a blood/plasma ratio of about 0.8.

Metabolism

In vitro studies with human liver homogenates have shown that budesonide is rapidly and extensively metabolized. Two major metabolites formed via cytochrome P450 (CYP) isoenzyme 3A4 (CYP3A4) catalyzed biotransformation have been isolated and identified as 16α-hydroxyprednisolone and 6β-hydroxybudesonide. The corticosteroid activity of each of these two metabolites is less than 1% of that of the parent compound. No qualitative differences between the in vitro and in vivo metabolic patterns have been detected. Negligible metabolic inactivation was observed in human lung and serum preparations.

Excretion/Elimination

The 22R form of budesonide was preferentially cleared by the liver with systemic clearance of 1.4 L/min vs. 1.0 L/min for the 22S form. The terminal half-life, 2 to 3 hours, was the same for both epimers and was independent of dose. Budesonide was excreted in urine and feces in the form of metabolites. Approximately 60% of an intravenous radiolabeled dose was recovered in the urine. No unchanged budesonide was detected in the urine.

Special Populations

No clinically relevant pharmacokinetic differences have been identified due to race, sex, or advanced age.

Geriatric

The pharmacokinetics of PULMICORT FLEXHALER in geriatric patients have not been specifically studied.

Pediatric

Following intravenous dosing in pediatric patients age 10-14 years, plasma half-life was shorter than in adults (1.5 hours vs. 2.0 hours in adults). In the same population following inhalation of budesonide via a pressurized metered-dose inhaler, absolute systemic availability was similar to that in adults.

Peak steady-state plasma concentrations of budesonide delivered via PULMICORT FLEXHALER in children and adolescents with asthma (n=14) occurred at approximately 15 to 30 minutes post-dose and averaged 0.4 and 1.5 nmol/L at doses of 180 mcg once daily and 360 mcg twice daily, respectively.

Nursing Mothers

The disposition of budesonide when delivered by inhalation from a dry powder inhaler at doses of 200 or 400 mcg twice daily for at least 3 months was studied in eight lactating women with asthma from 1 to 6 months postpartum. Systemic exposure to budesonide in these women appears to be comparable to that in non-lactating women with asthma from other studies. Breast milk obtained over eight hours post-dose revealed that the maximum concentration of budesonide for the 400 and 800 mcg doses was 0.39 and 0.78 nmol/L, respectively, and occurred within 45 minutes after dosing. The estimated oral daily dose of budesonide from breast milk to the infant is approximately 0.007 and 0.014 mcg/kg/day for the two dose regimens used in this study, which represents approximately 0.3% to 1% of the dose inhaled by the mother. Budesonide levels in plasma samples obtained from five infants at about 90 minutes after breastfeeding (and about 140 minutes after drug administration to the mother) were below quantifiable levels (<0.02 nmol/L in four infants and <0.04 nmol/L in one infant) [see Use In Specific Populations (8.2)].

Renal or Hepatic Insufficiency

There are no data regarding the specific use of PULMICORT FLEXHALER in patients with hepatic or renal impairment. Reduced liver function may affect the elimination of corticosteroids. The pharmacokinetics of budesonide were affected by compromised liver function as evidenced by a doubled systemic availability after oral ingestion. The intravenous pharmacokinetics of budesonide were, however, similar in cirrhotic patients and in healthy subjects.

Drug-Drug Interactions

Inhibitors of cytochrome P450 enzymes

Ketoconazole: Ketoconazole, a strong inhibitor of cytochrome P450 (CYP) isoenzyme 3A4 (CYP3A4), the main metabolic enzyme for corticosteroids, increased plasma levels of orally ingested budesonide [see Warnings and Precautions (5.7), Drug Interactions (7.1)].

Cimetidine: At recommended doses, cimetidine, a nonspecific inhibitor of CYP enzymes, had a slight but clinically insignificant effect on the pharmacokinetics of oral budesonide.

13 NONCLINICAL TOXICOLOGY

13.1 Carcinogenesis, Mutagenesis, Impairment of Fertility

In a 104-week oral study in Sprague-Dawley rats, a statistically significant increase in the incidence of gliomas was observed in male rats receiving an oral dose of 50 mcg/kg/day (approximately 0.3 times the MRHDID in adults and children 6 to 17 years of age on a mcg/m^2 basis). No tumorigenicity was seen in male rats at oral doses up to 25 mcg/kg (approximately 0.2 times the MRHDID in adults and children 6 to 17 years of age, on a mcg/m^2 basis) and in female rats at oral doses up to 50 mc/kg (approximately 0.3 times, the MRHDID doses in adults and children 6 to 17 years of age, respectively, on a mcg/m^2 basis). In two additional two-year studies in male Fischer and Sprague-Dawley rats, budesonide caused no gliomas at an oral dose of 50 mcg/kg (approximately 0.3 times the MRHDID in adults and children 6 to 17 years of age, respectively, on a mcg/m^2 basis). However, in the male Sprague-Dawley rats, budesonide caused a statistically significant increase in the incidence of hepatocellular tumors at an oral dose of 50 mcg/kg (approximately 0.3 times the MRHDID in adults and children 6 to 17 years of age on a mcg/m2 basis). The concurrent reference corticosteroids (prednisone and triamcinolone acetonide) in these two studies showed similar findings.

There was no evidence of a carcinogenic effect when budesonide was administered orally for 91 weeks to mice at doses up to 200 mcg/kg/day (approximately 0.7 times the MRHDID in adults and children 6 to 17 years of age on a mcg/m^2 basis). Budesonide was not mutagenic or clastogenic in six different test systems: Ames Salmonella/microsome plate test, mouse micronucleus test, mouse lymphoma test, chromosome aberration test in human lymphocytes, sex-linked recessive lethal test in Drosophila melanogaster, and DNA repair analysis in rat hepatocyte culture.

Fertility and reproductive performance were unaffected in rats at subcutaneous doses up to 80 mcg/kg (approximately 0.5 times the MRHDID in adults on a mcg/m2 basis). At a subcutaneous dose of 20 mcg/kg/day (approximately 0.1 times the maximum recommended daily inhalation dose in adults on a mcg/m2 basis), decreases in maternal body weight gain, prenatal viability, and viability of the young at birth and during lactation were observed. No such effects were noted at 5 mcg/kg (approximately 0.03 times the MRHDID in adults on a mcg/m2 basis).

14 CLINICAL STUDIES

14.1 Asthma

The safety and efficacy of PULMICORT FLEXHALER were evaluated in two 12-week, double-blind, randomized, parallel-group, placebo-controlled clinical studies conducted at sites in the United States and Asia involving 1137 patients aged 6 to 80 years with mild to moderate asthma. Study 1 evaluated PULMICORT FLEXHALER 180 mcg, PULMICORT TURBUHALER 200 mcg, and placebo, each administered as 1 inhalation once daily or 2 inhalations twice daily in patients 18 years of age and older with mild to moderate asthma previously treated with inhaled corticosteroids. The delivered dose of PULMICORT FLEXHALER 180 mcg and PULMICORT TURBUHALER 200 mcg are the same; each delivers 160 mcg from the mouthpiece. Study 2 evaluated PULMICORT FLEXHALER 90 mcg, 2 inhalations once daily or 4 inhalations twice daily, PULMICORT TURBUHALER 200 mcg, 1 inhalation once daily or 2 inhalations twice daily, and placebo in pediatric patients aged 6 to 17 years with mild to moderate asthma. Both of the studies had a 2-week placebo treatment run-in period followed by a 12-week randomized treatment period. The primary endpoint was the difference between baseline and the mean of the treatment-period FEV1 (adults) or FEV1 % predicted (children).

Patients ≥ 18 years of age and older (Study 1)

This study enrolled 621 patients aged ≥18 to 80 years with mild-to-moderate asthma (mean baseline % predicted FEV1 64.3%) whose symptoms were previously controlled on inhaled corticosteroids. Mean change from baseline in FEV1 in the PULMICORT FLEXHALER 180 mcg, 2 inhalations twice-daily group was 0.28 liters, as compared to 0.10 liters in the placebo group (p<0.001). Secondary endpoints of morning and evening peak expiratory flow rate, daytime asthma symptom severity, nighttime asthma symptom severity, daily rescue medication use, and the percentage of patients who met predefined asthma related withdrawal criteria showed differences from baseline favoring PULMICORT FLEXHALER over placebo (p<0.001).

12-Week Trial in Adult Patients with Mild to Moderate Asthma (Study 1) Mean Change from Baseline in FEV1 (L)

Footnote: PULMICORT TURBUHALER; a different PULMICORT DPI. Statistical model is analysis of covariance with treatment and region (US/Asia) as factors and the baseline value as the covariate.

Patients 6 to 17 years of age (Study 2)

This study enrolled 516 patients aged 6 to 17 years with mild asthma (mean baseline % predicted FEV1 84.9%). The study population included patients previously treated with inhaled corticosteroids for no more than 30 days before the study began (4%) and patients who were naïve to inhaled corticosteroids (96%). Mean change from baseline in % predicted FEV1 during the 12-week treatment period in the PULMICORT FLEXHALER 90 mcg, 4 inhalations twice daily treatment group was 5.6 compared with 0.2 in the placebo group (p<0.001). Secondary endpoints of morning and evening PEF showed differences from baseline favoring PULMICORT FLEXHALER over placebo (p<0.001).

12-Week Trial in Pediatric Patients With Mild Asthma (Study 2) Mean Change from Baseline in Percent Predicted FEV1

Footnote: PULMICORT TURBUHALER; a different PULMICORT DPI. Statistical model is analysis of covariance with treatment and region (US/Asia) as factors and the baseline value as the covariate.

16 HOW SUPPLIED/STORAGE AND HANDLING

Product: 50090-7867

NDC: 50090-7867-0 120 AEROSOL, POWDER in a INHALER / 1 in a CARTON

17 PATIENT COUNSELING INFORMATION

Patients being treated with PULMICORT FLEXHALER should receive the following information and instructions. This information is intended to aid the patient in the safe and effective use of the medication. It is not a disclosure of all possible adverse or intended effects. For proper use of PULMICORT FLEXHALER and to attain maximum improvement, the patient should read and follow the accompanying FDA Approved Patient Labeling.

17.1 Oral Candidiasis

Patients should be advised that localized infections with Candida albicans occurred in the mouth and pharynx in some patients. If oropharyngeal candidiasis develops, it should be treated with appropriate local or systemic (i.e., oral) antifungal therapy while still continuing therapy with PULMICORT FLEXHALER, but at times therapy with PULMICORT FLEXHALER may need to be temporarily interrupted under close medical supervision. Rinsing the mouth after inhalation is advised [see Warnings and Precautions (5.1)].

17.2 Not for Acute Symptoms

PULMICORT FLEXHALER is not meant to relieve acute asthma symptoms and extra doses should not be used for that purpose. Acute symptoms should be treated with an inhaled, short-acting beta2-agonist such as albuterol (the physician should provide the patient with such medication and instruct the patient in how it should be used).

Patients should be instructed to notify their physician immediately if they experience any of the following:

Decreasing effectiveness of inhaled, short-acting beta2-agonists

Need for more inhalations than usual of inhaled, short-acting beta2-agonists

Significant decrease in lung function as outlined by the physician

Patients should not stop therapy with PULMICORT FLEXHALER without physician/provider guidance since symptoms may recur after discontinuation [see Warnings and Precautions (5.1)].

17.3 Hypersensitivity Including Anaphylaxis

Hypersensitivity reactions including anaphylaxis, rash, contact dermatitis, urticaria, angioedema, and bronchospasm have been reported with use of PULMICORT FLEXHALER. Discontinue PULMICORT FLEXHALER if such reactions occur [see Contraindications (4), Warnings and Precautions (5.3), Adverse Reactions (6)].

PULMICORT FLEXHALER contains small amounts of lactose, which contains trace levels of milk proteins. It is possible that cough, wheezing, or bronchospasm may occur in patients who have a severe milk protein allergy [see Contraindications (4)].

17.4 Immunosuppression

Patients who are on immunosuppressant doses of corticosteroids should be warned to avoid exposure to chickenpox or measles and, if exposed, to consult their physician without delay. Patients should be informed of potential worsening of existing tuberculosis, fungal, bacterial, viral, or parasitic infections, or ocular herpes simplex [see Warnings and Precautions (5.4)].

17.5 Hypercorticism and Adrenal Suppression

Patients should be advised that PULMICORT FLEXHALER may cause systemic corticosteroid effects of hypercorticism and adrenal suppression. Additionally, patients should be instructed that deaths due to adrenal insufficiency have occurred during and after transfer from systemic corticosteroids. Patients should taper slowly from systemic corticosteroids if transferring to PULMICORT FLEXHALER [see Warnings and Precautions (5.5, 5.6)].

17.6 Reduction in Bone Mineral Density

Patients who are at an increased risk for decreased BMD should be advised that the use of corticosteroids may pose an additional risk [see Warnings and Precautions (5.8)].

17.7 Reduced Growth Velocity

Patients should be informed that orally inhaled corticosteroids, including budesonide inhalation powder, may cause a reduction in growth velocity when administered to pediatric patients. Physicians should closely follow the growth of children and adolescents taking corticosteroids by any route [see Warnings and Precautions (5.9)].

17.8 Ocular Effects

Long-term use of inhaled corticosteroids may increase the risk of some eye problems (cataracts or glaucoma); regular eye examinations should be considered [see Warnings and Precautions (5.10)].

17.9 Use Daily

Patients should be advised to use PULMICORT FLEXHALER at regular intervals, since its effectiveness depends on regular use. Maximum benefit may not be achieved for 1 to 2 weeks or longer after starting treatment. If symptoms do not improve in that time frame or if the condition worsens, patients should be instructed to contact their physician.

17.10 How to Use Pulmicort Flexhaler

Patients should be carefully instructed on the use of this drug product to assure optimal dose delivery. The patient may not sense the presence of any medication entering their lungs when inhaling from PULMICORT FLEXHALER. This lack of sensation does not mean that they did not get the medication. They should not repeat their inhalation even if they did not feel the medication when inhaling [see Patient Information].

PATIENT INFORMATION

PULMICORT FLEXHALER™ (bew DEH so nide) 180 mcg

(budesonide inhalation powder, 180 mcg)

PULMICORT FLEXHALER™ 90 mcg

(budesonide inhalation powder, 90 mcg)

Important Note: This medicine is to only be inhaled through the mouth (by oral inhalation only).

Read the Patient Information that comes with PULMICORT FLEXHALER before you start using it and each time you get a refill. There may be new information. This leaflet does not take the place of talking to your healthcare provider about your medical condition or treatment.

What is PULMICORT FLEXHALER?

PULMICORT FLEXHALER is an inhaled corticosteroid medicine. PULMICORT FLEXHALER is used for long-term (maintenance) treatment of asthma and to prevent asthma symptoms in adults and children 6 years of age and older.

Inhaled corticosteroids help to decrease inflammation in the lungs. Inflammation in the lungs can lead to asthma symptoms.

PULMICORT FLEXHALER helps reduce inflammation and helps keep the airways open to reduce asthma symptoms.

PULMICORT FLEXHALER does not treat the symptoms of a sudden asthma attack. Always have a short-acting beta2-agonist medicine (rescue inhaler) with you to treat sudden symptoms. If you do not have an inhaled, short-acting bronchodilator, call your healthcare provider to have one prescribed for you.

It is not known if PULMICORT FLEXHALER is safe and effective in children younger than 6 years of age.

Who should not use PULMICORT FLEXHALER?

Do not use PULMICORT FLEXHALER:

•to treat sudden severe symptoms of asthma.•if you have a severe allergy to milk proteins. PULMICORT FLEXHALER contains a small amount of lactose (milk sugar). People with severe allergies to milk protein may have symptoms of an allergic reaction with PULMICORT FLEXHALER including: cough, wheezing, trouble breathing or feeling like your throat is closing.

What should I tell my healthcare provider before using PULMICORT FLEXHALER?

Before using PULMICORT FLEXHALER, tell your healthcare provider if you:

•have any allergies. See the section “Who should not use PULMICORT FLEXHALER”. There is a complete list of ingredients in PULMICORT FLEXHALER at the end of this leaflet.•have or had chicken pox or measles, or have recently been near anyone with chicken pox or measles.•have or had tuberculosis of your respiratory tract.•have certain kinds of serious infections that have not been treated, including:•fungal infections•bacterial infections•viral infections•parasitic infections•herpes simplex infection of the eye (ocular herpes simplex)

PULMICORT FLEXHALER may not be right for people who have or had any of these types of infections.

•have liver problems•have decreased bone mineral density.

You are at risk for decreased bone mineral density if you:

•are inactive for a long period of time•have a family history of osteoporosis•are a woman going through menopause or are past menopause (“the change of life”)•smoke or use tobacco•do not eat well (poor nutrition)•are elderly•take bone thinning medicines (such as anticonvulsant medicines or corticosteroids) for a long time.•have eye problems such as increased pressure in the eye, glaucoma, or cataracts•are planning to have surgery•are pregnant or plan to become pregnant. It is not known if PULMICORT FLEXHALER may harm your unborn baby•are breast-feeding or plan to breast-feed. PULMICORT FLEXHALER can pass into breast milk. You and your healthcare provider should decide if you will use PULMICORT FLEXHALER or breast-feed

Tell your healthcare provider about all the medicines you take, including prescription and non-prescription medicines, vitamins, and herbal supplements. Using PULMICORT FLEXHALER with certain other medicines may affect each other causing side effects.

Especially tell your healthcare provider if you take:

•a corticosteroid medicine•anti-seizure medicine (anticonvulsants)•medicines that suppress your immune system (immunosuppressant)•ketoconazole (Nizoral), other medicines that affect how your liver works.

Ask your healthcare provider or pharmacist if you are not sure if your medicine is one listed above.

Know the medicines you take. Keep a list of them and show it to your healthcare provider and pharmacist when you get a new medicine.

How should I use PULMICORT FLEXHALER?

Use PULMICORT FLEXHALER exactly as prescribed by your healthcare provider. You must use PULMICORT FLEXHALER regularly for it to work.

•PULMICORT FLEXHALER comes in two strengths. Your healthcare provider has prescribed the strength that is best for you.•Be sure you know the difference between PULMICORT FLEXHALER and any other inhaled medicines that are prescribed for you, including what you use them for (prescribed use) and what they look like.•Do not stop using PULMICORT FLEXHALER, even if your symptoms get better. Your healthcare provider will change your medicines as needed.•Do not change or stop any medicines used to control or treat your breathing problems, unless your healthcare provider tells you to.•Rinse your mouth with water and spit the water out after each dose of PULMICORT FLEXHALER. Do not swallow the water. This will lessen the chance of getting a fungal infection (thrush) in the mouth.•If you miss a dose, just take your next regularly scheduled dose when it is due. Do not use PULMICORT FLEXHALER more often or use more puffs than you have been prescribed.•Make sure you always have a short-acting beta2-agonist medicine with you. Use your short acting beta2-agonist medicine if you have breathing problems between doses of PULMICORT FLEXHALER or if a sudden asthma attack happens. Call your healthcare provider right away if:∘your short-acting rescue medicine does not work as well for relieving asthma symptoms.∘you need to use your short-acting rescue medicines more often than usual.∘your breathing problems worsen with PULMICORT FLEXHALER.

If you use another inhaled medicine by mouth to treat your asthma, talk with your healthcare provider for instructions about when to use the other medicine and when to use your PULMICORT FLEXHALER.

•If you have used corticosteroid medicines for a long time and the dose is now being lowered or stopped, you should carry a medical alert card. The medical alert card should state that you may need increased corticosteroids during times of stress or during an asthma attack that does not get better with bronchodilator medicines.•Your healthcare provider may check your breathing, do blood tests and eye exams during treatment with PULMICORT FLEXHALER.•Be sure to read, understand and follow the detailed Patient Instructions for Use at the end of this leaflet. These Instructions for Use tell you how to prime and use your PULMICORT FLEXHALER the right way.

What are the possible side effects of PULMICORT FLEXHALER?

PULMICORT FLEXHALER can cause serious side effects, including:

•thrush (candida), a fungal infection in your mouth and throat. Tell your healthcare provider if you have any redness or white colored patches in your mouth or throat.•worsening of asthma or sudden asthma attacks.•allergic reactions. Tell your healthcare provider or get medical help right away if you have:∘skin rash, redness or swelling∘severe itching∘swelling of the face, mouth, and tongue∘trouble breathing or swallowing∘chest pain∘anxiety (feeling of doom)•Immune system effects and a higher chance of infections. You are more likely to get infections if you take medicines that weaken your immune system. Avoid contact with people who have contagious diseases such as chicken pox or measles while using PULMICORT FLEXHALER. Symptoms of infection may include: fever, pain, aches, chills, feeling tired, nausea and vomiting. Tell your healthcare provider about any signs of infection while you are using PULMICORT FLEXHALER.•Adrenal insufficiency. Adrenal insufficiency is a condition in which the adrenal glands do not make enough steroid hormones. Symptoms of adrenal insufficiency include: tiredness, weakness, nausea and vomiting and low blood pressure.•Decrease in bone mineral density. Your healthcare provider should check you for this during treatment with PULMICORT FLEXHALER.•Slowed or delayed growth problems in children. A child’s growth should be checked regularly while using PULMICORT FLEXHALER.•Eye problems, including glaucoma and cataracts. You should have regular eye exams while using PULMICORT FLEXHALER.•Increased wheezing right after taking PULMICORT FLEXHALER. Always have a short-acting beta2-agonist medicine (rescue inhaler) with you to treat sudden wheezing.

Call your healthcare provider or get medical help right away if you have symptoms of any of the serious side effects listed above.

Common side effects reported by patients using PULMICORT FLEXHALER include:

•sore nose and throat•stuffy nose•runny nose•nausea•hay fever•viral infections of the upper respiratory tract•viral irritation and inflammation of the stomach and intestine (gastroenteritis). Symptoms may include stomach area pain, diarrhea, nausea and vomiting, loss of appetite, headaches, and weakness.•ear infections

Tell your healthcare provider about any side effect that bothers you or that does not go away.

These are not all of the side effects of PULMICORT FLEXHALER. Ask your healthcare provider or pharmacist for more information.

Call your healthcare provider for medical advice about side effects. You may report side effects to the Safety Call Center 1-888-994-8116 or FDA at 1-800-FDA-1088 or www.fda.gov/medwatch.

How should I store PULMICORT FLEXHALER?

Store PULMICORT FLEXHALER at 68° to 77°F (20° to 25°C).

•Keep PULMICORT FLEXHALER dry.•Keep your PULMICORT FLEXHALER with the cover tightly in place when not in use.

Keep your PULMICORT FLEXHALER and all medicines out of the reach of children.

General Information about PULMICORT FLEXHALER

Medicines are sometimes prescribed for conditions that are not mentioned in Patient Information Leaflets. Do not use PULMICORT FLEXHALER for a condition for which it was not prescribed. Do not give PULMICORT FLEXHALER to other people, even if they have the same symptoms that you have. It may harm them.

This Patient Information leaflet summarizes the most important information about PULMICORT FLEXHALER. If you would like more information, talk with your healthcare provider. You can ask your pharmacist or healthcare provider for information about PULMICORT FLEXHALER that is written for health professionals.

For more information, go to pulmicortflexhaler.com or call 1- 800-236-9933.

What are the ingredients in PULMICORT FLEXHALER?

Active ingredient: budesonide

Inactive ingredient: lactose

Patient Instructions for Use

How to use your PULMICORT FLEXHALER

Parts of your PULMICORT FLEXHALER

Figure 1

Priming PULMICORT FLEXHALER:

Before you use a new PULMICORT FLEXHALER for the first time, you must prime it.

To prime your PULMICORT FLEXHALER, follow the steps below:

•Hold the inhaler by the brown grip so that the white cover points upward (upright position). With the other hand, turn the white cover and lift it off (see Figure 2).•Continue to hold your PULMICORT FLEXHALER upright as shown in Figure 1. Use your other hand to hold the inhaler in the middle. Do not hold the inhaler at the top of the mouthpiece.•Twist the brown grip as far as it will go in one direction and then fully back again in the other direction until it stops (it does not matter which way you turn it first). You will hear a “click” during one of the twisting movements (see Figures 3 and 4).•Repeat Step 3. Your PULMICORT FLEXHALER is now primed. You are ready to load your first dose.

You do not have to prime your PULMICORT FLEXHALER again after this even if you do not use it for a long period of time.

1 Loading a dose

•Hold your PULMICORT FLEXHALER upright as described above. With your other hand, twist the white cover and lift it off (see Figure 2).

Figure 2

•Continue to hold your PULMICORT FLEXHALER upright to be sure that the right dose of medicine is loaded.•Use your other hand to hold the inhaler in the middle. Do not hold the mouthpiece when you load the inhaler.•Twist the brown grip fully in one direction as far as it will go. Twist it fully back again in the other direction as far as it will go (it does not matter which way you turn it first) [see Figure 3].

Figure 3

•You will hear a “click” during one of the twisting movements (see Figure 4).

Figure 4

•PULMICORT FLEXHALER will only give one dose at a time, no matter how often you click the brown grip, but the dose indicator will continue to move (advance). This means that if you continue to move the brown grip, it is possible for the indicator to show fewer doses or zero doses even if more doses are left in the inhaler.•Do not shake the inhaler after loading it.

Figure 5

2 Inhaling a dose

•Turn your head away from the inhaler and breathe out (exhale). If you accidentally blow into your inhaler after loading a dose, follow the instructions for loading a new dose.•Place the mouthpiece in your mouth and close your lips around the mouthpiece. Breathe in (inhale) deeply and forcefully through the inhaler (see Figure 5).•You may not sense the presence of any medication entering your lungs when inhaling from PULMICORT FLEXHALER. This lack of sensation does not mean that you did not get the medication. You should not repeat your inhalations even if you did not feel the medication when inhaling.•Do not chew or bite on the mouthpiece.•Remove the inhaler from your mouth and exhale. Do not blow or exhale into the mouthpiece.•If more than one dose is prescribed repeat the steps above.•When you are finished taking your dose place the white cover back on the inhaler and twist shut.•Rinse your mouth with water after each dose to decrease your risk of getting thrush. Do not swallow the water.

Reading the Dose Indicator Window

•The label on the box or cover will tell you how many doses are in your PULMICORT FLEXHALER.•Your PULMICORT FLEXHALER has a dose indicator window just below the mouthpiece. The dose indicator tells you about how many doses are left in the inhaler. Look at the middle of the window to find out about how many doses are left in your inhaler (see Figure 6).

Figure 6

•The dose indicator is connected to the turning grip and moves (counts down) every time a dose is loaded. It is not likely that you will see the dose indicator move with each dose.You can usually see the indicator move each time you use about 5 doses.•

The dose indicator starts with either the number 60 or 120 when full, depending upon the strength of the inhaler. The indicator is marked in intervals of 10 doses. Markings are either with numbers or dashes (alternating), counting down to “0”.

60 Dose Inhaler |  |  | 120 Dose Inhaler
 | 20 |  |  | 80 |  | Dose indicator starts at 60 or 120 depending on strength (90 mcg or 180 mcg) of the inhaler and counts down to 0.
 | -- |  |  | -- |  | Dose indicator starts at 60 or 120 depending on strength (90 mcg or 180 mcg) of the inhaler and counts down to 0.
 | 40 |  |  | 100 |  | Dose indicator starts at 60 or 120 depending on strength (90 mcg or 180 mcg) of the inhaler and counts down to 0.
 | -- |  |  | -- |  | Dose indicator starts at 60 or 120 depending on strength (90 mcg or 180 mcg) of the inhaler and counts down to 0.
 | 60 |  |  | 120 |  | Dose indicator starts at 60 or 120 depending on strength (90 mcg or 180 mcg) of the inhaler and counts down to 0.
. |  |  |  |  |  | Dose indicator starts at 60 or 120 depending on strength (90 mcg or 180 mcg) of the inhaler and counts down to 0.

Figure 7

•Do not put your PULMICORT FLEXHALER in water (do not immerse it) to find out if it is empty. Check the dose indicator window to see how many doses are left.•Refill your PULMICORT FLEXHALER prescription before your medicine runs out. You will get a new inhaler each time you refill your prescription.

Cleaning your PULMICORT FLEXHALER

•Keep your PULMICORT FLEXHALER clean and dry at all times. Do not immerse it in water.•Wipe the outside of the mouthpiece one time each week with a dry tissue.•Do not use water or liquids when cleaning the mouthpiece.•Do not try to remove the mouthpiece or twist it.

Do not use your PULMICORT FLEXHALER if it has been damaged or if the mouthpiece has become detached. Talk to your healthcare provider or pharmacist if you have any problems with your PULMICORT FLEXHALER.

PULMICORT FLEXHALER is a trademark of the AstraZeneca group of companies.

©AstraZeneca 2007, 2008, 2010, 2016, 2019

Distributed by: Allegis Pharmaceuticals, Inc., Canton, MS 39046 USA

for: Rubicon Holdings Inc., Scottsdale, AZ 85254

Licensed by: CHEPLAPHARM Arzneimittel GmbH

Ziegelhof 24, 17489 Greifswald, Germany

Product of Sweden